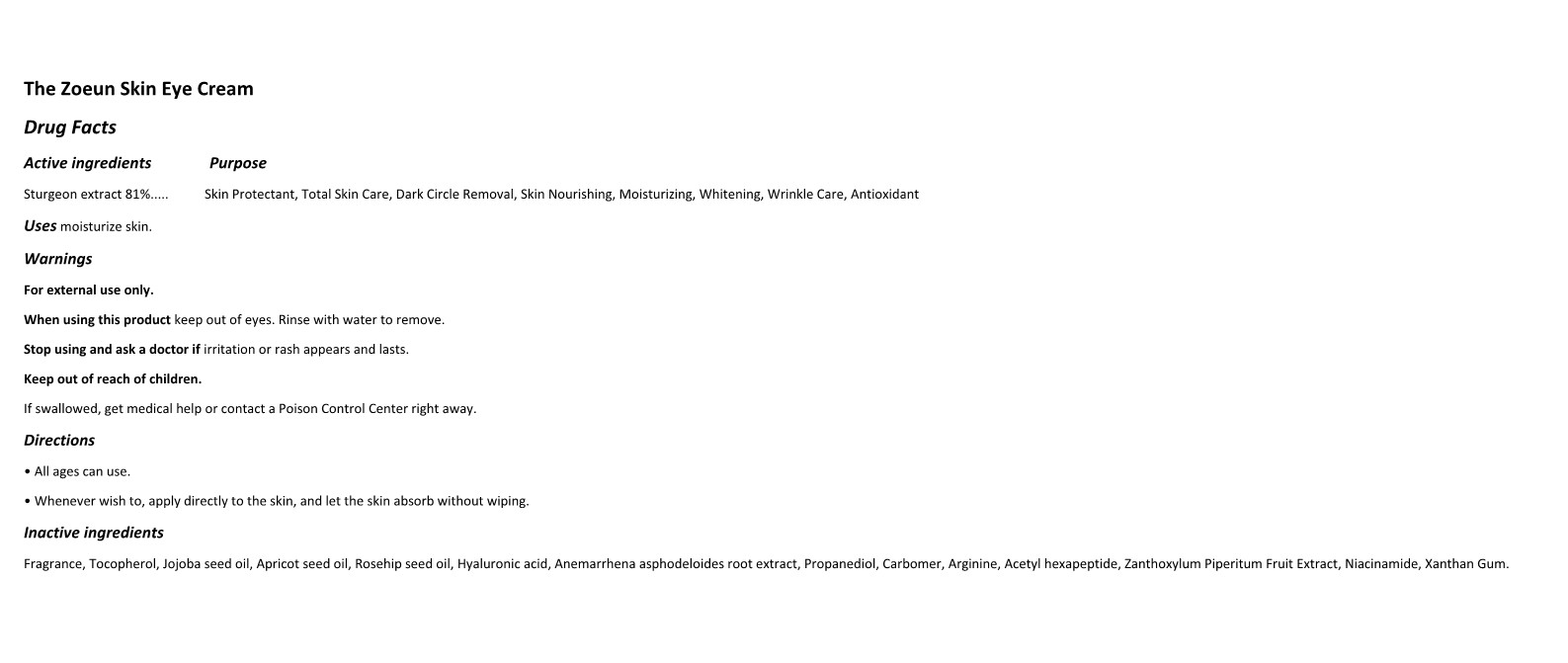 DRUG LABEL: The Zoeun Skin Eye Cream
NDC: 83636-202 | Form: CREAM
Manufacturer: Sturgeonbio Co.,Ltd.
Category: otc | Type: HUMAN OTC DRUG LABEL
Date: 20240115

ACTIVE INGREDIENTS: STURGEON, UNSPECIFIED 81 g/100 mL
INACTIVE INGREDIENTS: ZANTHOXYLUM PIPERITUM FRUIT PULP; TOCOPHEROL; ANEMARRHENA ASPHODELOIDES ROOT; ROSA MOSCHATA OIL; HYALURONIC ACID; PROPANEDIOL; ACETYL HEXAPEPTIDE-1; CARBOMER HOMOPOLYMER, UNSPECIFIED TYPE; JOJOBA OIL; ARGININE; NIACINAMIDE; FRAGRANCE 13576; APRICOT SEED OIL; XANTHAN GUM

83636-202 The Zoeun Skin Eye Cream

Active Ingredients

Sturgeon extract 81%

Purposes

Skin Protectant, Total Skin Care, Dark Circle Removal, Skin Nourishing, Moisturizing, Brightening, Wrinkle Care, Antioxidant

Uses

Dark Circle Removal, Moisturizing, Brightening, Wrinkle Care

Warnings

For external use only.

Warnings

When using this product keep out of eyes. Rinse with water to remove.

Warnings

Stop using and ask a doctor if irritation or rash appears and lasts.

Warnings

Keep out of reach of children.
If swallowed, get medical help or contact a Poison Control Center right away.

Directions

• All ages can use.

• Whenever wish to, apply directly to the skin, and let the skin absorb without wiping.

Inactive Ingredients

Fragrance, Tocopherol, Jojoba seed oil, Apricot seed oil, Rosehip seed oil, Hyaluronic acid, Anemarrhena asphodeloides root extract, Propanediol, Carbomer, Arginine, Acetyl hexapeptide, Zanthoxylum Piperitum Fruit Extract, Niacinamide, Xanthan Gum.